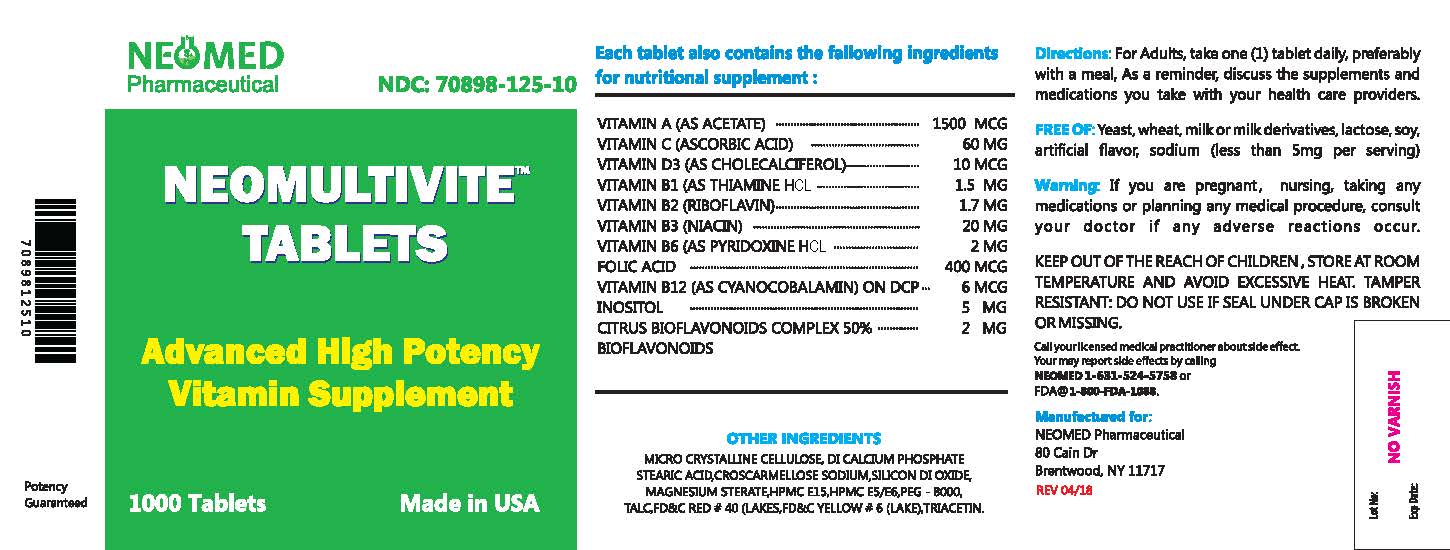 DRUG LABEL: NEOMULTIVITE
NDC: 70898-125 | Form: TABLET
Manufacturer: NEOMED PHARMACEUTICAL
Category: other | Type: DIETARY SUPPLEMENT
Date: 20180913

ACTIVE INGREDIENTS: VITAMIN A 1500 ug/1 1; ASCORBIC ACID 60 ug/1 1; CHOLECALCIFEROL 10 ug/1 1; THIAMINE 1.5 mg/1 1; RIBOFLAVIN 1.7 mg/1 1; NIACINAMIDE 20 mg/1 1; PYRIDOXINE HYDROCHLORIDE 2 mg/1 1; FOLIC ACID 400 ug/1 1; CYANOCOBALAMIN 6 ug/1 1; CITRUS BIOFLAVONOIDS 2 mg/1 1; INOSITOL 5 mg/1 1
INACTIVE INGREDIENTS: CROSCARMELLOSE SODIUM; MICROCRYSTALLINE CELLULOSE; CALCIUM PHOSPHATE, DIBASIC, ANHYDROUS; STEARIC ACID; SILICON DIOXIDE; TITANIUM DIOXIDE; MAGNESIUM STEARATE; TALC; POLYETHYLENE GLYCOLS; HYPROMELLOSES; TRIACETIN; FD&C RED NO. 40; FD&C YELLOW NO. 6

NEOMULTIVITE TABLETS
Advanced High Potency Vitamin Supplement
Multivitamin and Mineral Supplement

STATEMENT OF IDENTITY

SUPPLEMENT FACTS:

Serving Size: One Tablet

Each Tablet contains:
Vitamin A (as acetate) |  | 1500 mcg
Vitamin D3 (as cholecalciferol) |  | 10 mcg
Vitamin C (Ascorbic acid) |  | 60 mcg
Vitamin B1 (as thiamine HCl) |  | 1.5 mg
Vitamin B2 (as riboflavin) |  | 1.7 mg
Niacin (Vitamin B3) |  | 20 mg
Vitamin B6 (as pyridoxine HCl) |  | 2 mg
Folic acid |  | 400 mcg
Vitamin B12 (as cyanocobalamin) |  | 6 mcg
Citrus bioflavonoids complex 50% bio flavonoids |  | 2 mg
Inositol |  | 5 mg

- Other Ingredients: Di calcium phosphate, microcrystalline croscarmellose sodium, stearic acid, silicon dioxide, titanium dioxide (as color), polyethylene glycol, magnesium stearate, talc,triacetin, HPMC E15,HPMC E5/E6,FD&C RED #40 (LAKES),FD&C YELLOW # 6 (LAKE)

WARNINGS

CONTRAINDICATIONS

NEOMULTIVITE TABLETS contraindicated in patients with hypersensitivity to any of its components. Folic Acid is contraindicated in patients with untreated and uncomplicated pernicious anemia, and in those with anaphylactic sensitivity to folic acid.

Cyanocobalamin is contraindicated in patients with sensitivity to cobalt or to cyanocobalamin (Vitamin B12)

WARNING/PRECAUTIONS

Vitamin D supplementation should be used with caution in those with hypercalcemia or conditions that may lead to hypercalcemia such as hyperparathyroidism and those who form calcium-containing kidney stones. High doses of vitamin D can lead to elevated levels of calcium that reside in the blood and soft tissues. Bone pain, high blood pressure, formation of kidney stones, renal failure, and increased risk of heart disease can occur.

Avoid Over dosage. Keep out of the reach of children.

Information for Patients

Patients should be counseled to disclose all medical conditions, including use of all medications, vitamins and supplements, pregnancy, and breastfeeding.

Pediatric Use

Not recommended for pediatric use.

HEALTH CLAIM

DOSAGE AND ADMINISTRATION

Adults - Take one tablet daily with water, as a dietary supplement or as directed by a doctor.

HOW SUPPLIED

NEOMULTIVITE ; available in bottles of 1000 Tablets. 70898-125-10

Store at room temperature 15°-30°C (59°-86°F). Avoid excessive heat and moisture.

Distributed by:

Neomed Pharmaceutical
80 Cain Dr, Brentwood, NY 11717
Phone :631-524-5758

Email: info@neomedpharmaceutical.com

DISCLAIMER: This drug has not been found by FDA to be safe and effective, and this labeling has not been approved by FDA. For further information about unapproved drugs, click here.